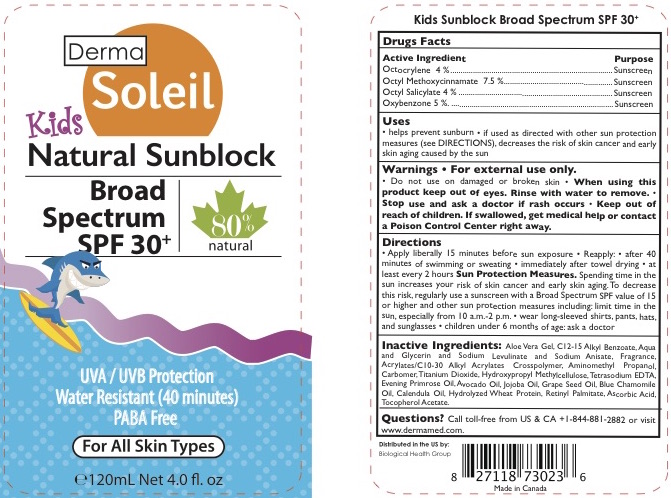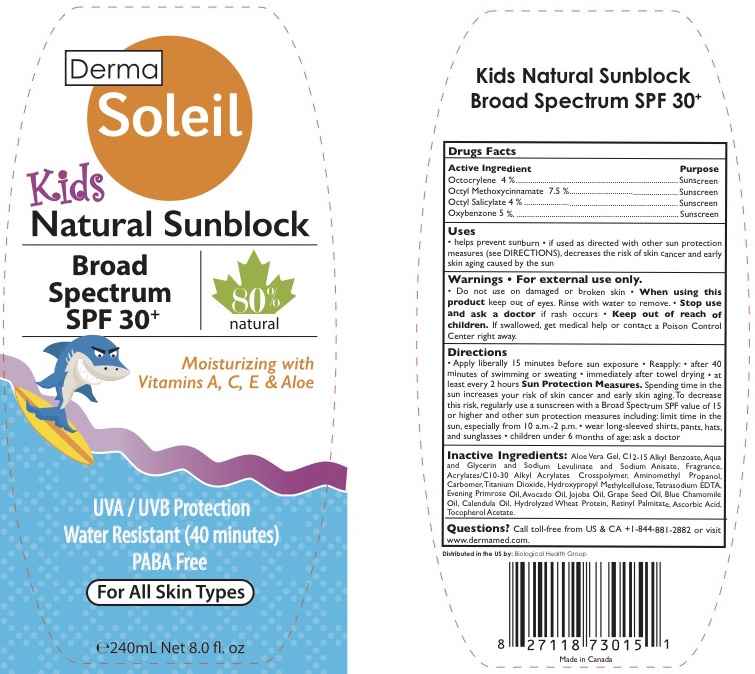 DRUG LABEL: DERMA SOLEIL KIDS NATURAL SUNBLOCK SPF 30
NDC: 69711-908 | Form: LOTION
Manufacturer: Biological Health Group
Category: otc | Type: HUMAN OTC DRUG LABEL
Date: 20200224

ACTIVE INGREDIENTS: OCTOCRYLENE 4 g/100 mL; OCTINOXATE 7.5 g/100 mL; OCTISALATE 4 g/100 mL; OXYBENZONE 5 g/100 mL
INACTIVE INGREDIENTS: VITAMIN A PALMITATE; ASCORBIC ACID; ALOE VERA LEAF; CARBOMER INTERPOLYMER TYPE A (55000 CPS); CALENDULA OFFICINALIS FLOWER; HYDROLYZED WHEAT PROTEIN (ENZYMATIC, 3000 MW); EVENING PRIMROSE OIL; SODIUM LEVULINATE; AMINOMETHYLPROPANOL; CARBOXYPOLYMETHYLENE; HYPROMELLOSES; EDETATE SODIUM; JOJOBA OIL; GLYCERYL CAPRYLATE; WATER; GRAPE SEED OIL; ALKYL (C12-15) BENZOATE; CHAMOMILE FLOWER OIL; .ALPHA.-TOCOPHEROL ACETATE; GLYCERIN; SODIUM ANISATE; CARBOMER COPOLYMER TYPE A (ALLYL PENTAERYTHRITOL CROSSLINKED); AVOCADO OIL; TITANIUM DIOXIDE

DERMA SOLEIL KIDS NATURAL SUNBLOCK SPF 30

ACTIVE INGREDIENT

Octocrylene 4%
Octyl Methoxycinnamate 7.5%,
Octyl Salicylate 4%,
Oxybenzone 5%

PURPOSE

Sunscreen

WHEN USING

Helps prevent sunburn
If used as directed with other sun protection measures (see DIRECTIONS), decreases the risk of skin cancer and early skin aging caused by the sun.

WARNINGS

For external use only.

Do not use on damaged or broken skin. Stop use and ask a doctor if rash occurs.

When using this product keep out of eyes. Rinse with water to remove.

Keep out of reach of children. If swallowed, get medical help or contact a poison control center right away.

INDICATIONS AND USAGE

• Apply liberally 15 minutes before sun exposure • Reapply: • after 40 minutes of swimming or sweating • immediately after towel drying • at least every 2 hours
Sun Protection Measures. Spending time in the sun increases your risk of skin cancer and early skin aging.To decrease this risk, regularly use a sunscreen with a Broad Spectrum SPF value of 15 or higher and other sun protection measures including: limit time in the sun, especially from 10 a.m.-2 p.m. • wear long-sleeved shirts, pants, hats, and sunglasses • children under 6 months of age: ask a doctor

INACTIVE INGREDIENT

Aloe Vera Gel, C12-15 Alkyl Benzoate, Aqua and Glycerin and Sodium Levulinate and Sodium Anisate, Fragrance, Acrylates/C10-30 Alkyl Acrylates Crosspolymer, Aminomethyl Propanol, Carbomer, Titanium Dioxide, Hydroxypropyl Methylcellulose, Tetrasodium EDTA, Evening Primrose Oil, Avocado Oil, Jojoba Oil, Grape Seed Oil, Blue Chamomile Oil, Calendula Oil, Hydrolyzed Wheat Protein, Retinyl Palmitate, Ascorbic Acid, Tocopherol Acetate.